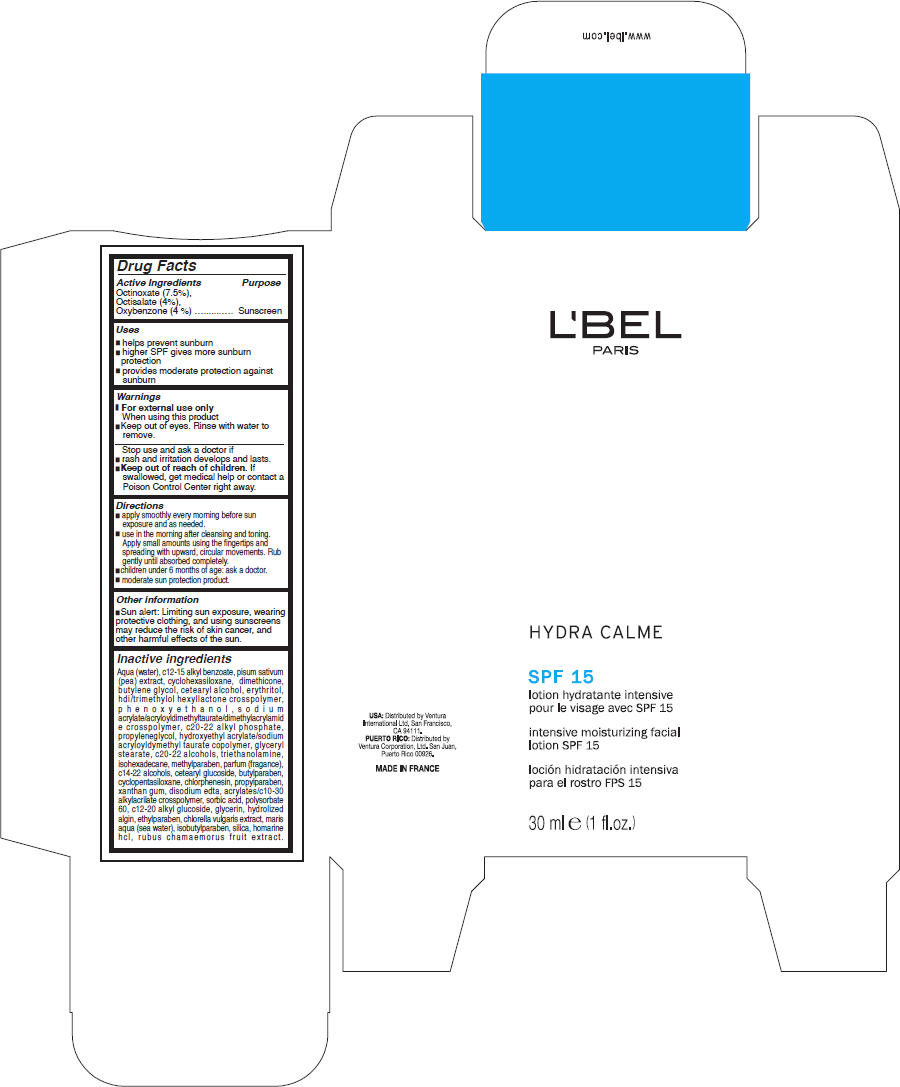 DRUG LABEL: LBEL 
NDC: 13537-088 | Form: LOTION
Manufacturer: Ventura International LTD
Category: otc | Type: HUMAN OTC DRUG LABEL
Date: 20100810

ACTIVE INGREDIENTS: Octinoxate 2.25 mg/30 mL; Octisalate 1.2 mg/30 mL; Oxybenzone 1.2 mg/30 mL
INACTIVE INGREDIENTS: water; c12-15 alkyl benzoate; snow pea; cyclomethicone 6; dimethicone; butylene glycol; cetostearyl alcohol; erythritol; phenoxyethanol; propylene glycol; glyceryl monostearate; trolamine; isohexadecane; methylparaben; butylparaben; cyclomethicone 5; chlorphenesin; propylparaben; xanthan gum; edetate disodium; sorbic acid; polysorbate 60; glycerin; ethylparaben; isobutylparaben; silicon dioxide

L'BEL
PARIS
HYDRA CALME

Drug Facts

Active Ingredients

Octinoxate (7.5%), Octisalate (4%), Oxybenzone (4 %)

Purpose

Sunscreen

Uses

- helps prevent sunburn
- higher SPF gives more sunburn protection
- provides moderate protection against sunburn

Warnings

- For external use only

When using this product

- Keep out of eyes. Rinse with water to remove.

Stop use and ask a doctor if

- rash and irritation develops and lasts.

- Keep out of reach of children. If swallowed, get medical help or contact a Poison Control Center right away.

Directions

- apply smoothly every morning before sun exposure and as needed.
- use in the morning after cleansing and toning. Apply small amounts using the fingertips and spreading with upward, circular movements. Rub gently until absorbed completely.
- children under 6 months of age: ask a doctor.
- moderate sun protection product.

Other information

- Sun alert: Limiting sun exposure, wearing protective clothing, and using sunscreens may reduce the risk of skin cancer, and other harmful effects of the sun.

Inactive ingredients

Aqua (water), c12-15 alkyl benzoate, pisum sativum (pea) extract, cyclohexasiloxane, dimethicone, butylene glycol, cetearyl alcohol, erythritol, hdi/trimethylol hexyllactone crosspolymer, phenoxyethanol, sodium acrylate/acryloyldimethyltaurate/dimethylacrylamide crosspolymer, c20-22 alkyl phosphate, propyleneglycol, hydroxyethyl acrylate/sodium acryloyldymethyl taurate copolymer, glyceryl stearate, c20-22 alcohols, triethanolamine, isohexadecane, methylparaben, parfum (fragance), c14-22 alcohols, cetearyl glucoside, butylparaben, cyclopentasiloxane, chlorphenesin, propylparaben, xanthan gum, disodium edta, acrylates/c10-30 alkylacrilate crosspolymer, sorbic acid, polysorbate 60, c12-20 alkyl glucoside, glycerin, hydrolized algin, ethylparaben, chlorella vulgaris extract, maris aqua (sea water), isobutylparaben, silica, homarine hcl, rubus chamaemorus fruit extract.

USA: Distributed by Ventura
International Ltd, San Francisco,
CA 94111.

PRINCIPAL DISPLAY PANEL - 30 ml Carton

L'BEL
PARIS

HYDRA CALME

SPF 15

intensive moisturizing facial
lotion SPF 15

30 ml e (1 fl.oz.)